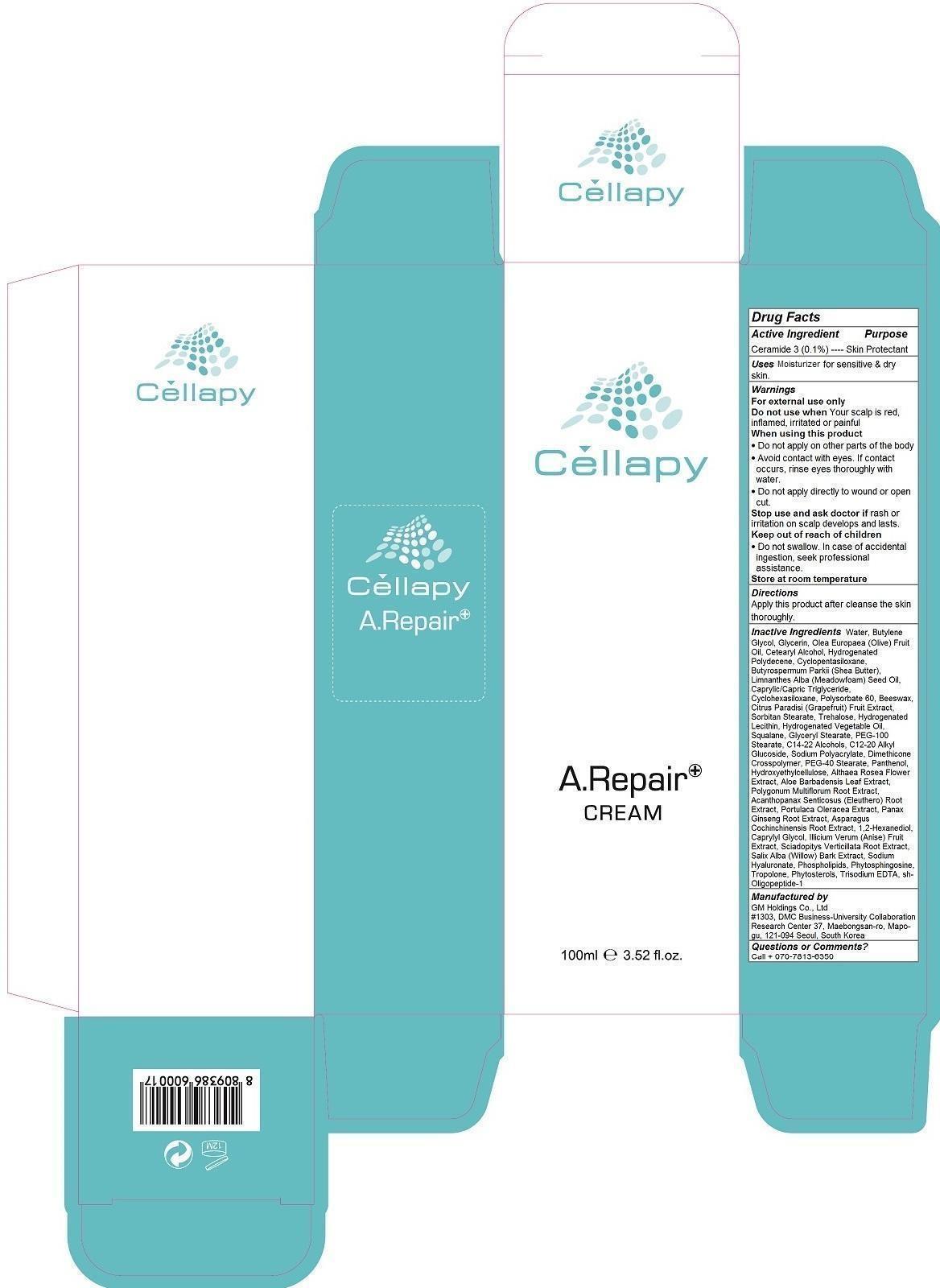 DRUG LABEL: Cellapy A Repair Cream
NDC: 69278-103 | Form: CREAM
Manufacturer: GM Holdings Co., Ltd
Category: otc | Type: HUMAN OTC DRUG LABEL
Date: 20200121

ACTIVE INGREDIENTS: CERAMIDE 3 0.1 1/100 mL
INACTIVE INGREDIENTS: WATER; BUTYLENE GLYCOL; GLYCERIN; OLIVE OIL; CETOSTEARYL ALCOHOL; HYDROGENATED POLYDECENE (550 MW); CYCLOMETHICONE 5; SHEA BUTTER; MEADOWFOAM SEED OIL; TRICAPRYLIN; CYCLOMETHICONE 6; POLYSORBATE 60; YELLOW WAX; GRAPEFRUIT; SORBITAN MONOSTEARATE; TREHALOSE; HYDROGENATED SOYBEAN LECITHIN; SQUALANE; GLYCERYL MONOSTEARATE; PEG-100 STEARATE; C14-22 ALCOHOLS; C12-20 ALKYL GLUCOSIDE; SODIUM POLYACRYLATE (8000 MW); PEG-40 STEARATE; PANTHENOL; HYDROXYETHYL CELLULOSE (100 MPA.S AT 2%); ALCEA ROSEA FLOWER; ALOE VERA LEAF; FALLOPIA MULTIFLORA ROOT; ELEUTHERO; PURSLANE; ASIAN GINSENG; ASPARAGUS COCHINCHINENSIS TUBER; 1,2-HEXANEDIOL; CAPRYLYL GLYCOL; STAR ANISE FRUIT; SCIADOPITYS VERTICILLATA ROOT; SALIX ALBA BARK; HYALURONATE SODIUM; OMEGA-3 FATTY ACIDS; PHYTOSPHINGOSINE; TROPOLONE; NEPIDERMIN

Cellapy A Repair Cream